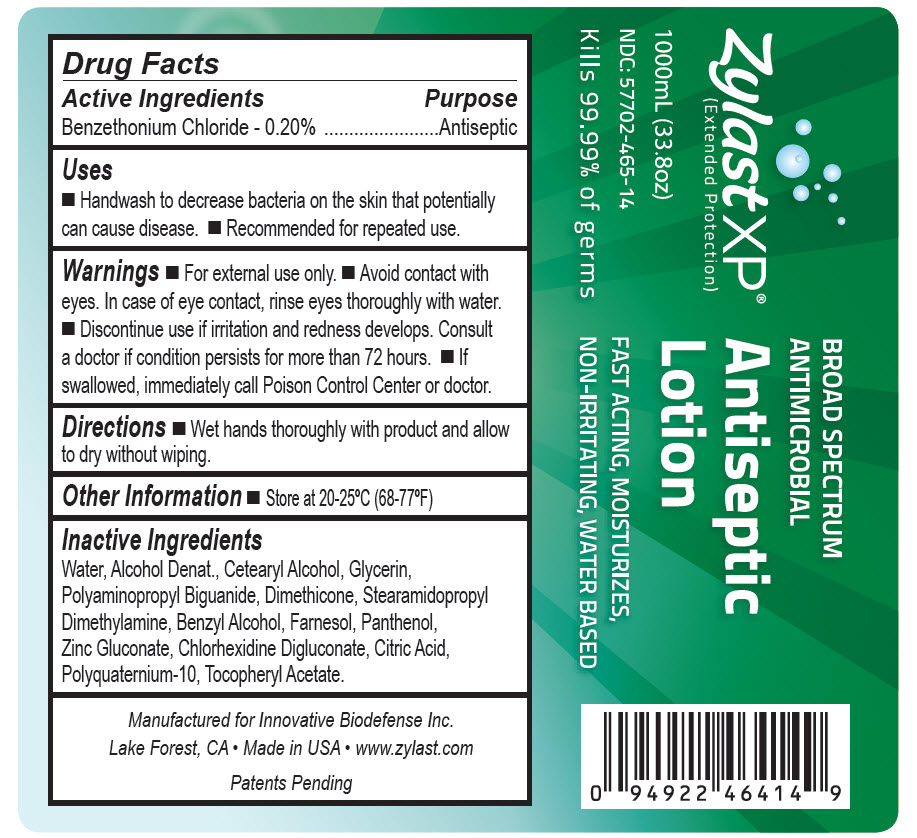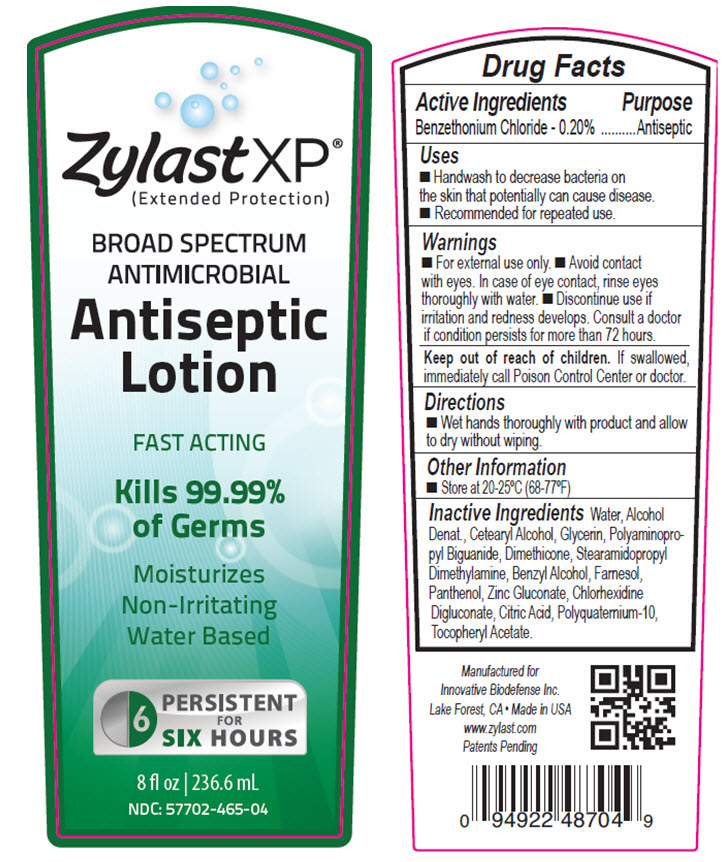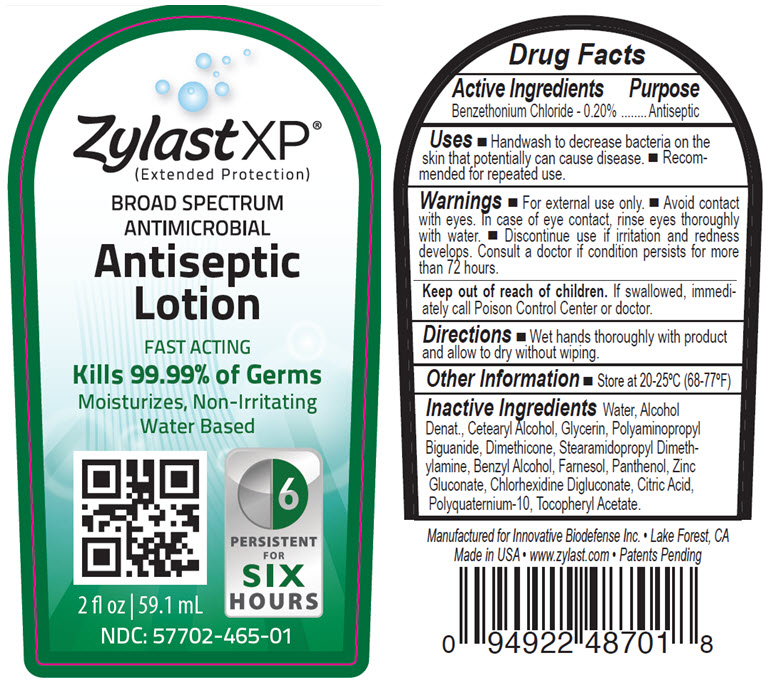 DRUG LABEL: Zylast XP Antiseptic
NDC: 57702-465 | Form: LOTION
Manufacturer: Bocchi Laboratories Inc.
Category: otc | Type: HUMAN OTC DRUG LABEL
Date: 20140331

ACTIVE INGREDIENTS: BENZETHONIUM CHLORIDE 2 mg/1 mL
INACTIVE INGREDIENTS: WATER; CETOSTEARYL ALCOHOL; GLYCERIN; POLIHEXANIDE; DIMETHICONE; STEARAMIDOPROPYL DIMETHYLAMINE; BENZYL ALCOHOL; FARNESOL; PANTHENOL; ZINC GLUCONATE; CHLORHEXIDINE GLUCONATE; CITRIC ACID MONOHYDRATE; .ALPHA.-TOCOPHEROL ACETATE

Zylast Antiseptic Lotion
Drug Facts

Active Ingredients

Benzethonium Chloride - 0.20%

Purpose

Antiseptic

Uses

- Handwash to decrease bacteria on the skin that potentially can cause disease.
- Recommended for repeated use.

Warnings

- For external use only.
- Avoid contact with eyes. In case of eye contact, rinse thoroughly with water.
- Discontinue use if irritation and redness develops. Consult a doctor if condition persists for more than 72 hours.
- If swallowed, immediately call Poison Control Center or doctor.

Directions

- Wet hands thoroughly with product and allow to dry without wiping.

Other Information

- Store at 20-25°C (68-77°F)

Inactive ingredients

Water, Alcohol Denat., Cetearyl Alcohol, Glycerin, Polyaminopropyl Biguanide, Dimethicone, Stearamidopropyl Dimethylamine, Benzyl Alcohol, Farnesol, Panthenol, Zinc Gluconate, Chlorhexidine Digluconate, Citric Acid, Polyquaternium-10, Tocopheryl Acetate.

Active Ingrdients

Benzethonium Chloride - 0.20%

Purpose

Antiseptic

Uses

- Handwash to decrease bacteria on the skin that potentially can cause disease.
- Recommended for repeated use.

Warnings

- For external use only.
- Avoid contact with eyes. In case of eye contact, rinse thoroughly with water.
- Discontinue use if irritation and redness develops. Consult a doctor if condition persists for more than 72 hours.
- If swallowed, immediately call Poison Control Center or doctor.

Keep out of reach of children.

If swallowed, immediately call Poison Control Center or doctor.

Directions

- Wet hands thoroughly with product and allow to dry without wiping.

Other Information

- Store at 20-25°C (68-77°F)

Inactive Ingredients

Water, Alcohol Denat., Cetearyl Alcohol, Glycerin, Polyaminopropyl Biguanide, Dimethicone, Stearamidopropyl Dimethylamine, Benzyl Alcohol, Farnesol, Panthenol, Zinc Gluconate, Chlorhexidine Digluconate, Citric Acid, Polyquaternium-10, Tocopheryl Acetate.

Package/Label Principal Display Panel

NDC 57702-465-14
Zylast XP
Extended Protection
Broad Spectrum
Antimicrobial
Antiseptic
1000mL (33.8oz)

Package/Label Principal Display Panel

NDC 57702-465-04
Zylast XP
Extended Protection
Broad Spectrum
Antimicrobial
Antiseptic
8 fl oz. 236.6 mL

Package/Label Principal Display Panel

NDC 57702-465-01
Zylast XP
Extended Protection
Broad Spectrum
Antimicrobial
Antiseptic
2 fl oz 59.1 mL